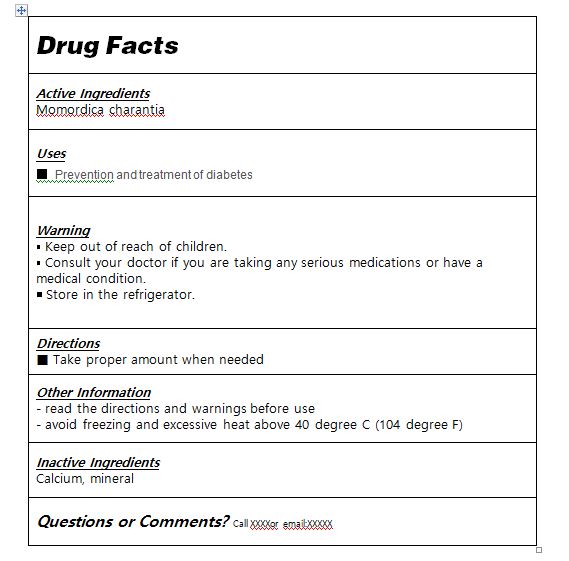 DRUG LABEL: Diabetes Out
NDC: 82265-0004 | Form: LIQUID
Manufacturer: CHANGJAE BENKO BIO Co., Ltd.
Category: otc | Type: HUMAN OTC DRUG LABEL
Date: 20220314

ACTIVE INGREDIENTS: MOMORDICA CHARANTIA FRUIT 0.5 g/1 mL
INACTIVE INGREDIENTS: MINERAL OIL

Drug Facts

ACTIVE INGREDIENT

Momordica charantia

PURPOSE

Prevention and treatment of diabetes

KEEP OUT OF REACH OF THE CHILDREN

INDICATIONS AND USAGE

Take proper amount when needed

WARNINGS

■ For external use only.

■ Do not use in eyes.

■ Stop use, ask doctor lf irritation occurs.

■ Keep out of reach of children.

DOSAGE AND ADMINISTRATION

for oral use only

INACTIVE INGREDIENT

Water, calcium, mineral etc.